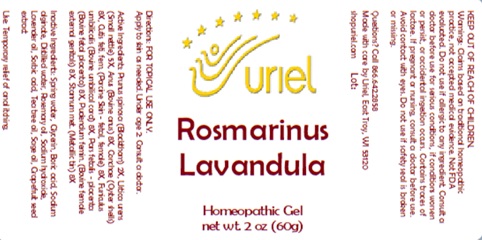 DRUG LABEL: Rosmarinus Lavandula
NDC: 48951-8436 | Form: GEL
Manufacturer: Uriel Pharmacy Inc.
Category: homeopathic | Type: HUMAN OTC DRUG LABEL
Date: 20250902

ACTIVE INGREDIENTS: SLOE 2 [hp_X]/1 g; URTICA URENS 5 [hp_X]/1 g; BEEF 8 [hp_X]/1 g; OSTREA EDULIS SHELL 8 [hp_X]/1 g; SUS SCROFA SKIN 8 [hp_X]/1 g; SUS SCROFA UMBILICAL CORD 8 [hp_X]/1 g; BOS TAURUS SOMATIC NERVE 8 [hp_X]/1 g; TIN 8 [hp_X]/1 g; BOS TAURUS PLACENTA 8 [hp_X]/1 g
INACTIVE INGREDIENTS: BORIC ACID; ROSEMARY OIL; SODIUM HYDROXIDE; TEA TREE OIL; SAGE OIL; CITRUS PARADISI SEED; GLYCERIN; LAVENDER OIL; SORBIC ACID; WATER; SODIUM ALGINATE

Rosmarinus Lavandula

INDICATIONS AND USAGE

Directions: FOR TOPICAL USE ONLY.

DOSAGE AND ADMINISTRATION

Apply to skin as needed. Under age 2: Consult a doctor.

ACTIVE INGREDIENT

Active Ingredients: Prunus spinosa (Blackthorn) 2X, Urtica urens (Small nettle) 5X, Anus (Bovine anus) 8X, Conchae (Oyster shells) 8X,Cutis feti. fem. (Porcine Skin - fetal, female) 8X, Funiculus umbilicalis (Bovine umbilical cord) 8X, Pudendum femin. (Bovine female external genitals) 8X, Stannum met. (Metallic tin) 8X, Pars fetalis - placenta (Bovine fetal placenta) 8X

INACTIVE INGREDIENT

Inactive Ingredients: Distilled water, Glycerin, Boric acid, Sodium alginate, Rosemary oil, Sodium hydroxide, Lavender oil, Sorbic acid, Tea tree oil, Sage oil, Grapefruit seed extract

Prepared using rhythmical processes.

PURPOSE

Use: Temporary relief of anal itching.

KEEP OUT OF REACH OF CHILDREN.

WARNINGS

Warnings: Claims based on traditional homeopathic practice, not accepted medical evidence. Not FDA evaluated. Do not use if allergic to any ingredient. Consult a doctor before use for serious conditions, if conditions worsen or persist, or accidental ingestion occurs. If pregnant or nursing, consult a doctor before use. Avoid contact with eyes. Do not use if safety seal is broken or missing.

Questions? Call 866.642.2858
Made with care by Uriel, East Troy, WI 53120
shopuriel.com Lot: